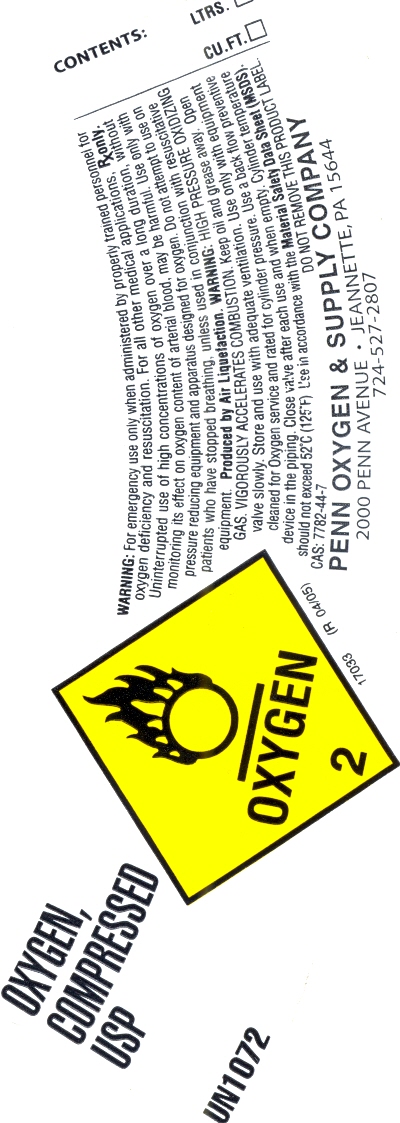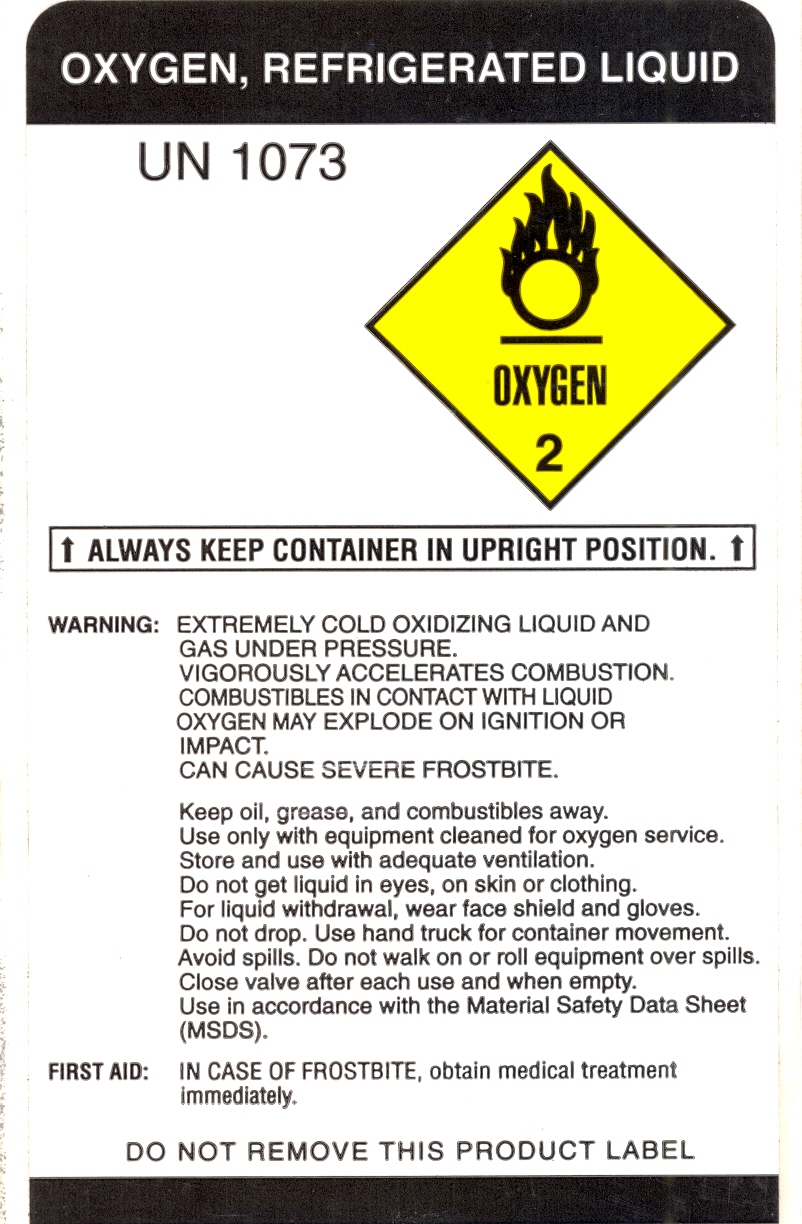 DRUG LABEL: Oxygen
NDC: 50558-001 | Form: GAS
Manufacturer: BGR Enterprises, Inc. dba Penn Oxygen & Supply Company
Category: prescription | Type: HUMAN PRESCRIPTION DRUG LABEL
Date: 20091120

ACTIVE INGREDIENTS: Oxygen 995 mL/1 L

Oxygen Compressed USP

PACKAGE LABEL

Enter section text here

OXYGEN, COMPRESSED USP UN1072 OXYGEN 2 17033 (R 04/05)
Contents: LTRS. Cu.Ft
Warning: For emergency use only when administered by properly trained personnel for oxygen deficiency and resuscitation. RX only. Uninterrupted use of high concentrations of Oxygen over a long duration, without monitory it's effect on Oxygen content of arterial blood, may be harmful. Use only with pressure reducing equipment and apparatus designed for Oxygen. Do not attempt to use on patients who have stopped breathing, unless used in conjunction with resuscitative equipment. Produce by Air Liquefaction. WARNING: HIGH PRESSURE OXIDIZING GAS VIGOROUSLY ACCELERATES COMBUSTION. Keep oil and grease away. Open valve slowly. Store and use with adequate ventilation. Use only with equipment cleaned for Oxygen. Service and rated for cylinder pressure.
Use a back flow preventative device in the piping. Close valve after each use and when empty. Cylinder temperatures should not exceed 52 degrees C or (125 degrees F). Use in accordance with the Material Safety Data Sheet (MSDS).
Do not remove this product label. Penn Oxygen and Supply Company 2000 Penn Avenue Jeannette, PA 15644

PACKAGE LABEL

Enter section text here

OXYGEN, REFRIGERATED LIQUID
UN1073
OXYGEN 2
ALWAYS KEEP CONTAINER IN UPRIGHT POSITION.
WARNING: EXTREMELY COLD OXIDIZING LIQUID AND GAS UNDER PRESSURE.
VIGOROUSLY ACCELERATES COMBUSTION.
COMBUSTIBLES IN CONTACT WITH LIQUID OXYGEN MAY EXPLODE ON IGNITION OR IMPACT.
CAN CAUSE SEVERE FROSTBITE.
KEEP OIL, GREASE, AND COMBUSTIBILES AWAY.
USE ONLY WITH EQUIPMENT CLEANED FOR OXYGEN SERVICE.
STORE AND USE WITH ADEQUATE VENTILATION.
DO NOT GET LIQUID IN EYES, ON SKIN, OR CLOTHING.
FOR LIQUID WITHDRAWAL, WEAR FACE SHIELD AND GLOVES.
DO NOT DROP. USE HAND TRUCK FOR CONTAINER MOVEMENT.
AVOID SPILLS. DO NOT WALK ON OR ROLL EQUIPMENT OVER SPILLS.
CLOSE VALVE AFTER EACH USE AND WHEN EMPTY.
USE IN ACCORDANCE WITH THE MATERIAL SAFETY DATA SHEET (MSDS).
FIRST AID: IN CASE OF FROSTBITE, OBTAIN MEDICAL TREATMENT IMMEDIATELY.
DO NOT REMOVE THIS PRODUCT LABEL 4513